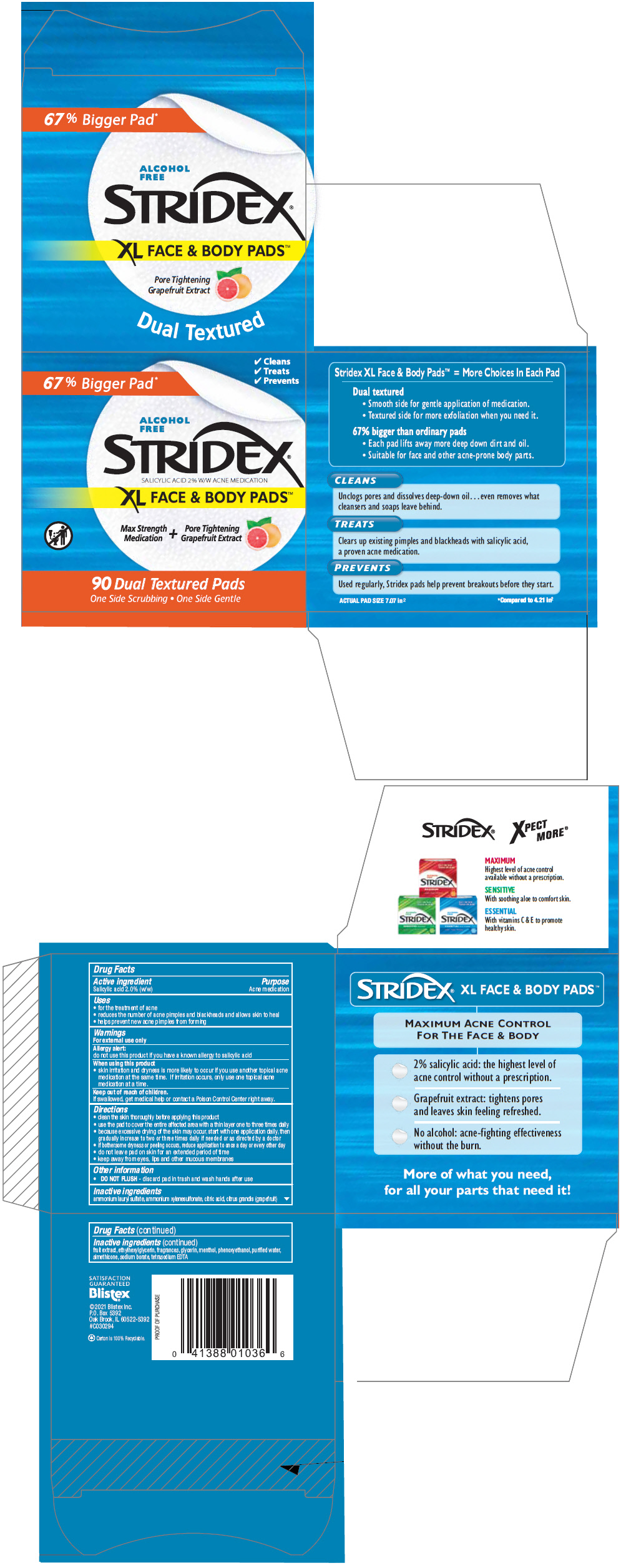 DRUG LABEL: Stridex XL Face and Body Pads
NDC: 10157-2114 | Form: LIQUID
Manufacturer: Blistex Inc
Category: otc | Type: HUMAN OTC DRUG LABEL
Date: 20241213

ACTIVE INGREDIENTS: Salicylic Acid 2 g/100 mL
INACTIVE INGREDIENTS: water; sodium borate; .ALPHA.-CHLOROHYDRIN; pummelo; ammonium lauryl sulfate; ammonium xylenesulfonate; citric acid monohydrate; phenoxyethanol; ETHYLHEXYLGLYCERIN; MENTHOL, UNSPECIFIED FORM; silicon dioxide; edetate sodium

Stridex® XL Face & Body Pads™

Drug Facts

Active ingredient

Salicylic acid 2.0% (w/w)

Purpose

Acne medication

Uses

- for the treatment of acne
- reduces the number of acne pimples and blackheads and allows skin to heal
- helps prevent new acne pimples from forming

Warnings

For external use only

Allergy alert

do not use this product if you have a known allergy to salicylic acid

When using this product

- skin irritation and dryness is more likely to occur if you use another topical acne medication at the same time. If irritation occurs, only use one topical acne medication at a time.

Keep out of reach of children.

If swallowed, get medical help or contact a Poison Control Center right away.

Directions

- clean the skin thoroughly before applying this product
- use the pad to cover the entire affected area with a thin layer one to three times daily
- because excessive drying of the skin may occur, start with one application daily, then gradually increase to two or three times daily if needed or as directed by a doctor
- if bothersome dryness or peeling occurs, reduce application to once a day or every other day
- do not leave pad on skin for an extended period of time
- keep away from eyes, lips and other mucous membranes

Other information

- DO NOT FLUSH - discard pad in trash and wash hands after use

Inactive ingredients

ammonium lauryl sulfate, ammonium xylenesulfonate, citric acid, citrus grandis (grapefruit) fruit extract, ethylhexylglycerin, fragrances, glycerin, menthol, phenoxyethanol, purified water, simethicone, sodium borate, tetrasodium EDTA

PRINCIPAL DISPLAY PANEL - 90 Pad Jar Carton

✓ Cleans
✓ Treats
✓ Prevents

67% Bigger Pad*

ALCOHOL
FREE

STRIDEX®
SALICYLIC ACID 2% W/W ACNE MEDICATION

XL FACE & BODY PADS™

Max Strength
Medication
+
Pore Tightening
Grapefruit Extract

90 Dual Textured Pads
One Side Scrubbing • One Side Gentle